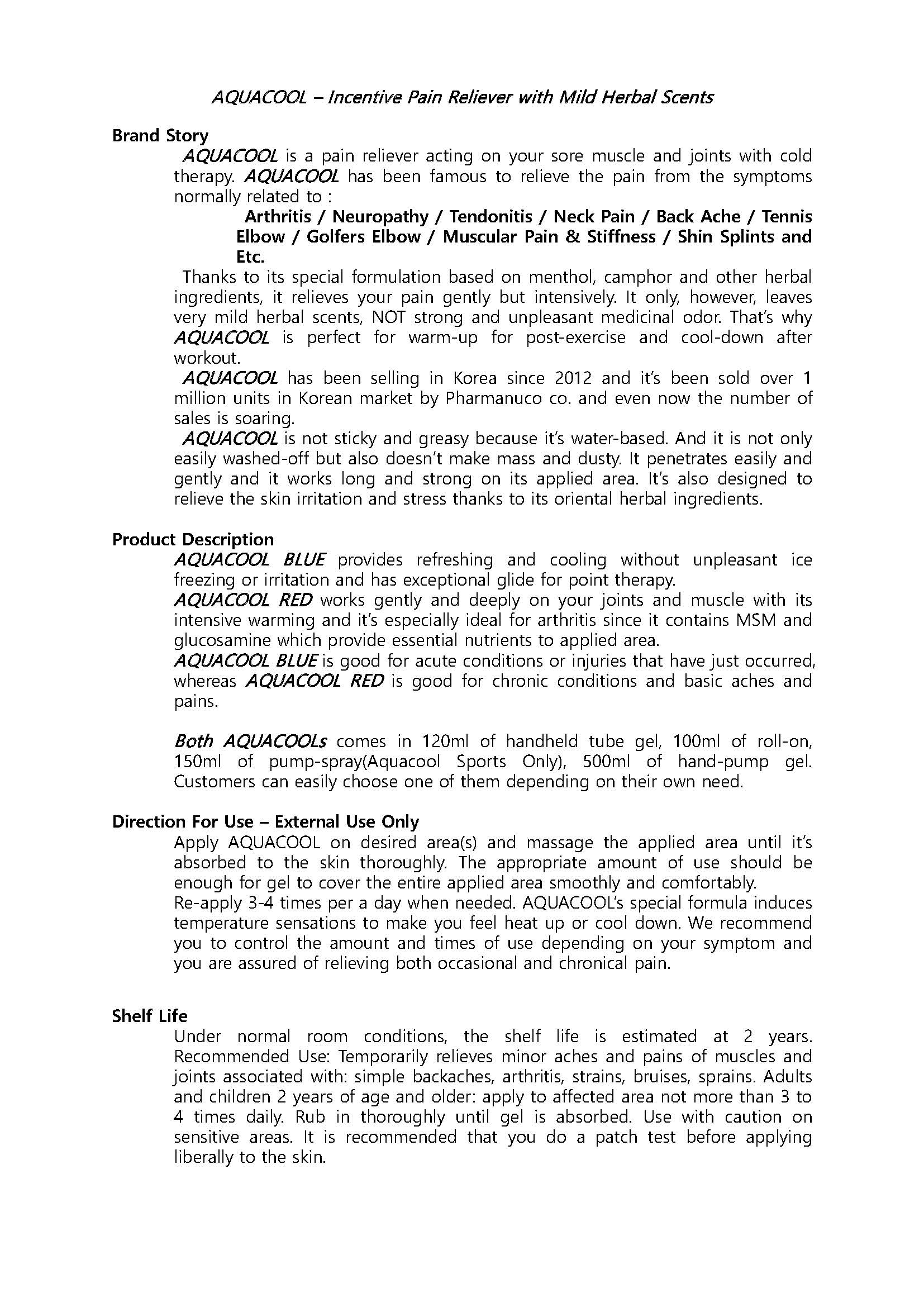 DRUG LABEL: AQUACOOL BLUE ROLL
NDC: 70759-0003 | Form: GEL
Manufacturer: Pharmanuco
Category: otc | Type: HUMAN OTC DRUG LABEL
Date: 20210309

ACTIVE INGREDIENTS: MENTHOL 3.2 g/100 mL
INACTIVE INGREDIENTS: GLYCYRRHIZA URALENSIS; WATER; GLYCERIN

Drug Facts

ACTIVE INGREDIENT

MENTHOL

INACTIVE INGREDIENT

WATER, ISOPROPYL ALCOHOL, GLYCERIN, GLYCYRRHIZA URALENSIS, CARBOMER, CAMPHOR, NaOH, CI 42090, METHYLPARABEN, CASTOR OIL

PURPOSE

To relieve pain

keep out of reach of the children

INDICATIONS AND USAGE

Apply proper amount to desired area(s) and massage the applied area until it's absorbed to the skin thoroughly.

DOSAGE AND ADMINISTRATION

for external use only

WARNINGS

1. Under normal room conditions, the shelf life is estimated at 2 years.
2. Recommended Use: Temporarily relieves minor aches and pains of muscles and joints associated with: simple backaches, arthritis, strains, bruises, sprains.
3. Adults and children 2 years of age and older: apply to affected area not more than 3 to 4 times daily.
4. Rub in thoroughly until gel is absorbed.
5. Use with caution on sensitive areas.
6. It is recommended that you do a patch test before applying liberally to the skin.